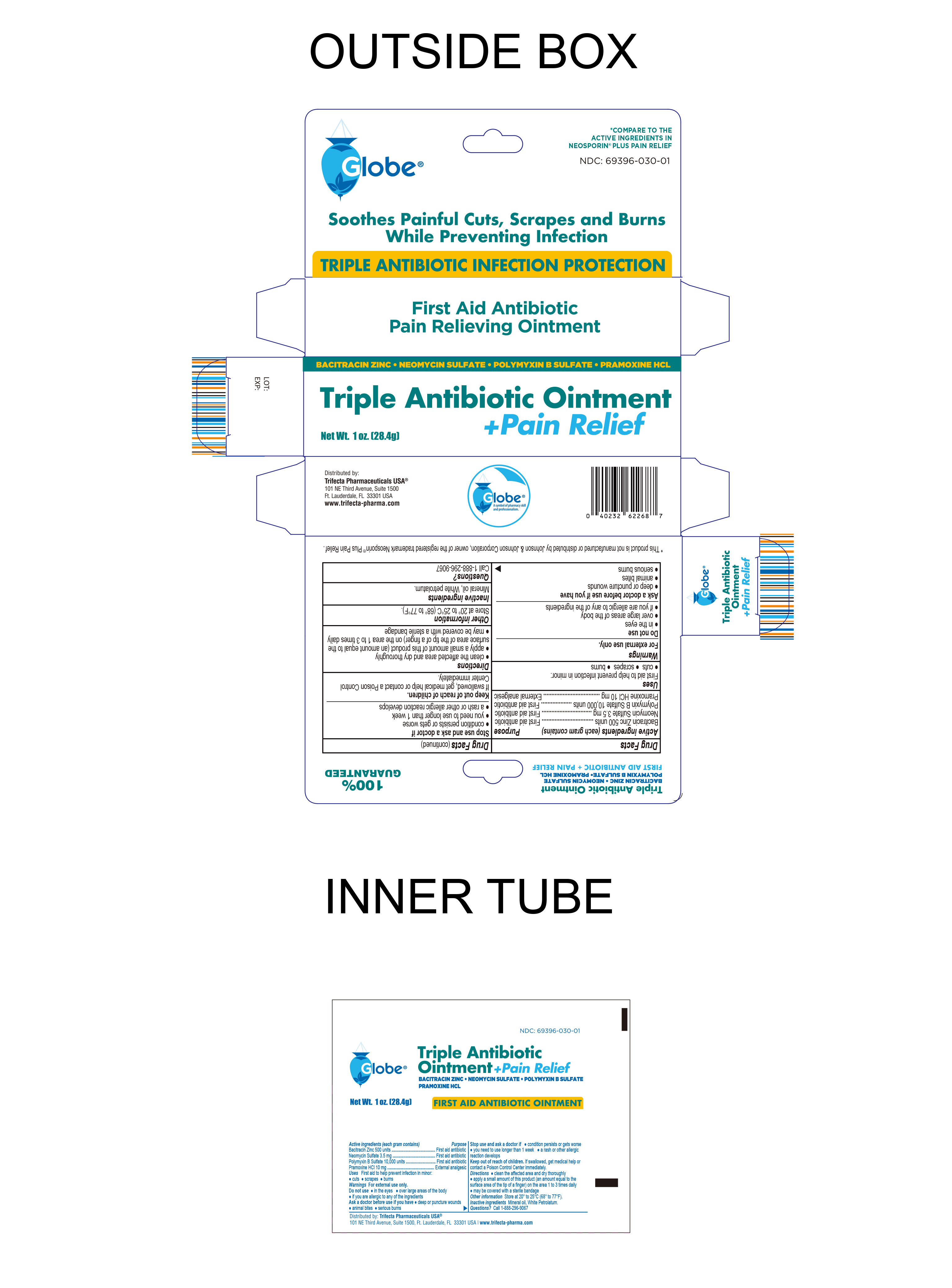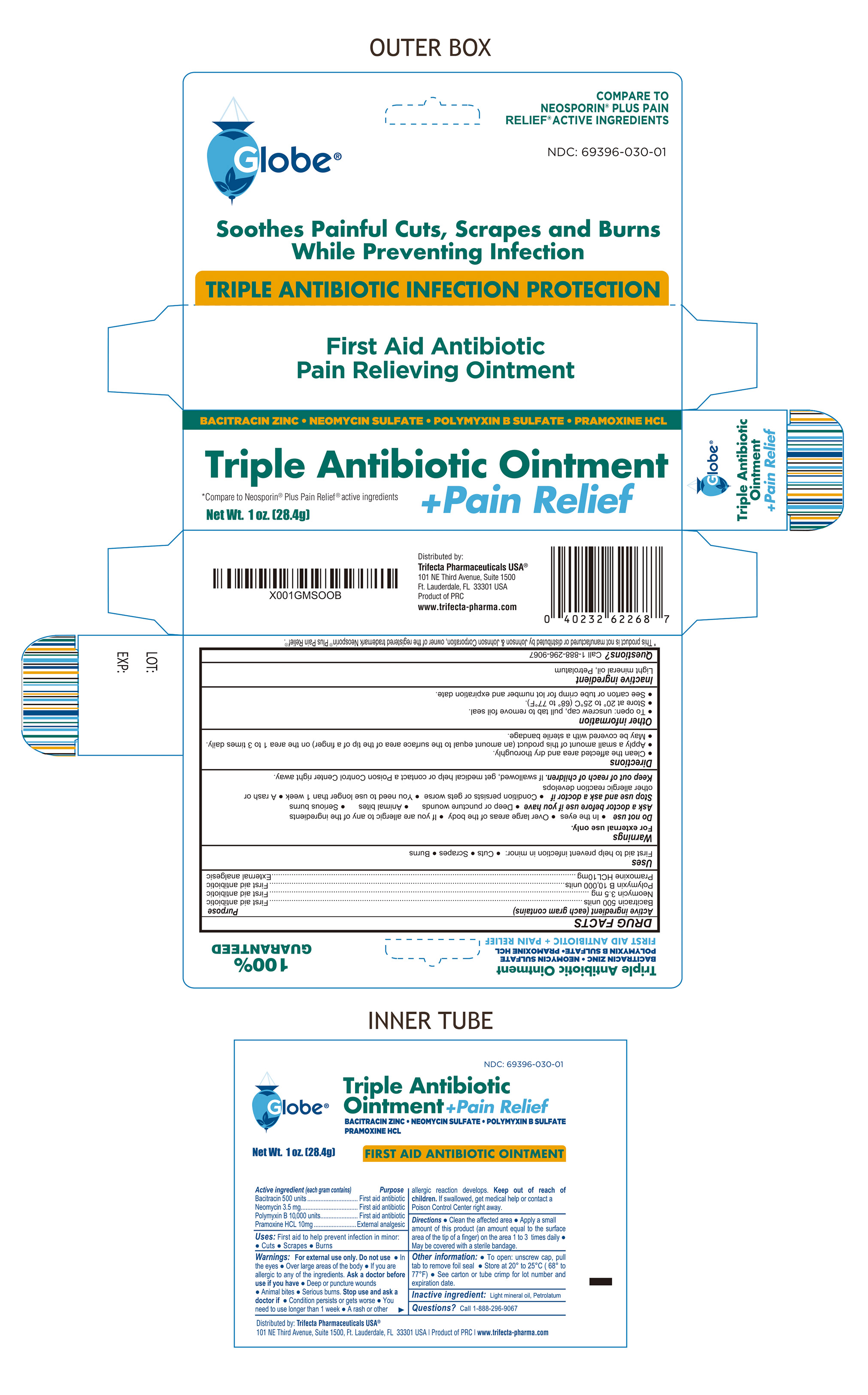 DRUG LABEL: Tripleantibioticointmentandpainrelief
NDC: 69396-030 | Form: OINTMENT
Manufacturer: Trifecta Pharmaceuticals USA
Category: otc | Type: HUMAN OTC DRUG LABEL
Date: 20251022

ACTIVE INGREDIENTS: BACITRACIN 500 [USP'U]/100 g; NEOMYCIN SULFATE 3.5 mg/100 g; PRAMOXINE HYDROCHLORIDE 10 mg/100 g; POLYMYXIN B SULFATE 10000 [USP'U]/100 g
INACTIVE INGREDIENTS: WHITE PETROLATUM; MINERAL OIL

Triple Antibiotic Ointment + Pain Relief

Active Ingredient

Bacitracin Zinc 500 Units

Purpose

First Aid Antibiotic

Active Ingredient

Neomycin 3.5mg

Purpose

First Aid Antibiotic

Active Ingredient

Polymyxin B 10,000 Units

Purpose

First Aid Antibiotic

Active Ingredient

Pramoxine HCL 10mg

Purpose

External Analgesic

Uses

First Aid to help prevent infection in minor:

- Cuts
- Scrapes
- Burns

Warnings

For external use only. Do not use:

- In eyes
- Over large areas of the body
- If you are allergic to any of the ingredients

Ask a Doctor before Use

Ask Doctor before use if you have:

- Deep or puncture wouns
- Animal bites
- Serious burns

Stop Use and ask a Doctor if:

- Condition persists or gets worse
- You need to use longer than 1 week
- A rash or other allergic reaction develops

Keep out of Reach of Children

If Swallowed, get medical help or contact a Poison Control Center right away

Directions

- Clean the affected area
- Apply a small amount of this product (an amount equal to the surface area of the tip of a finger) on the area 1 to 3 times daily
- May be covered with a sterile bandage

Other Information

- To Open: Unscrew cap, pull tab to remove foil seal
- Store at 20° to 25°C (68° to 77°F)
- See carton or tube crimp for lot number and expiration date

Inactive Ingredient:

mineral oil, white Petrolatum

Questions?

Call 1-888-296-9067

Distributed By:

Trifecta Pharmaceuticals USA ®

101 NE Third Avenue, Suite 1500

Fort Lauderdale, FL. 33301 USA

www.trifecta-pharma.com